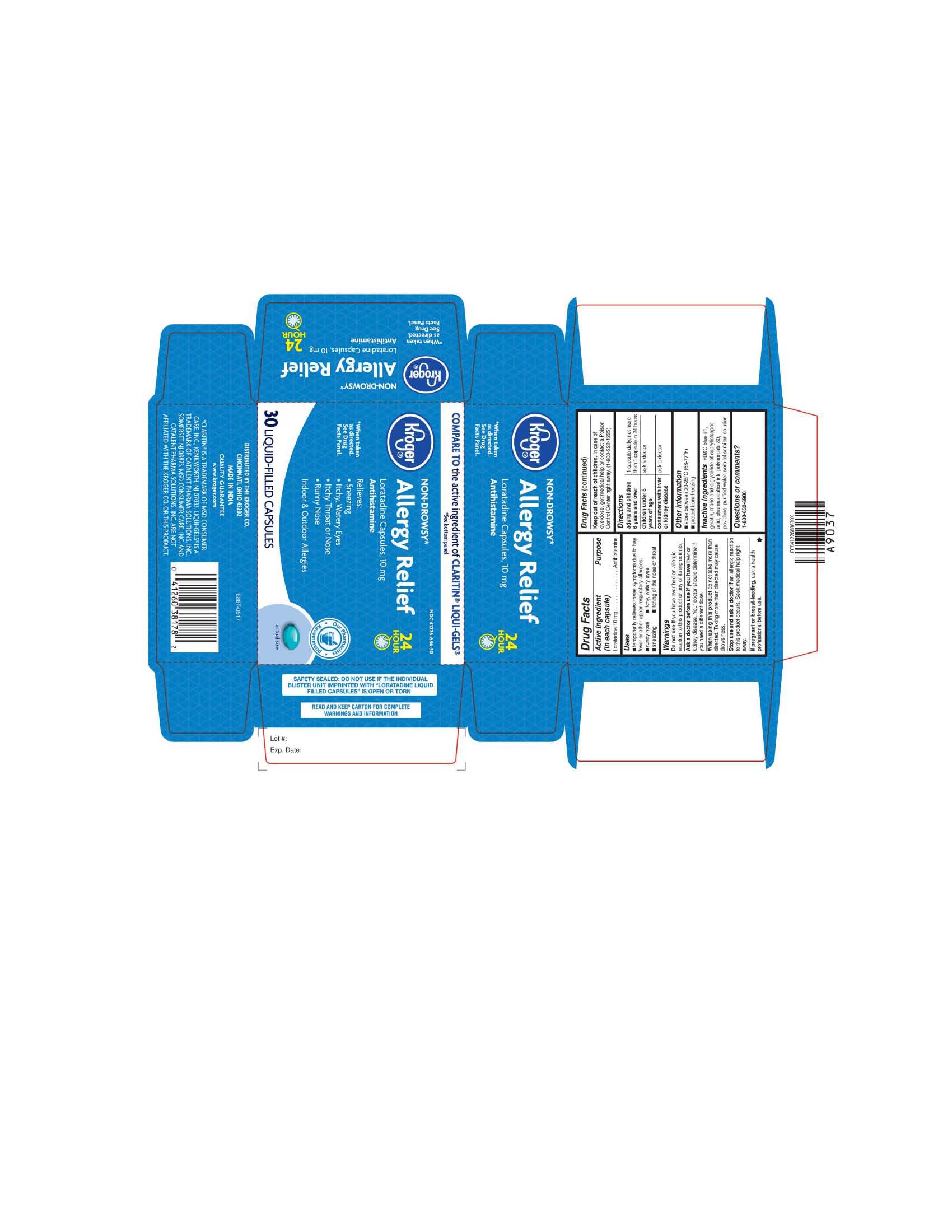 DRUG LABEL: LORATADINE
NDC: 41226-686 | Form: CAPSULE, LIQUID FILLED
Manufacturer: KROGER COMPANY
Category: otc | Type: HUMAN OTC DRUG LABEL
Date: 20251229

ACTIVE INGREDIENTS: LORATADINE 10 mg/1 1
INACTIVE INGREDIENTS: FD&C BLUE NO. 1; GELATIN; POLYSORBATE 80; POVIDONE; WATER; SORBITOL; CAPRYLIC/CAPRIC MONO/DIGLYCERIDES

KROGER 686T

ACTIVE INGREDIENT

LORATADINE 10MG

DO NOT USE IF YOU HAVE EVER HAD AN ALLERGIC REACTION TO THIS PRODUCT OR ANY OF ITS INGREDIENTS.

WHEN USING THIS PRODUCT DO NOT TAKE MORE THAN DIRECTED. TAKING MORE THAN DIRECTED MAY CAUSE DROWSINESS.

STOP USE AND ASK A DOCTOR IF AN ALLERGIC REACTION TO THIS PRODUCT OCCURS. SEEK MEDICAL HELP RIGHT AWAY.

IF PREGNANT OR BREAST FEEDING, ASK A HEALTH PROFESSIONAL BEFORE USE.

PURPOSE

ANTIHISTAMINE

INDICATIONS AND USAGE

TEMPORARILY RELIEVES THESE SYMPTOMS DUE TO HAY FEVER OR OTHR UPPER RESPIRATORY ALLERGIES:

RUNNY NOSE

ITCHY, WATERY EYES

SNEEZING

ITCHING OF THE NOSE OR THROAT

KEEP OUT OF REACH OF CHILDREN

IN CASE OF OVERDOSE, GET MEDICAL HELP OR CONTACT A POISON CONTROL CENTER RIGHT AWAY.

DOSAGE AND ADMINISTRATION

ADULTS AND CHILDREN 6 YEARS AND OVER: 1 CAPSULE DAILY; NOT MORE THAN 1 CAPSULE IN 24 HOURS.

CHILDREN UNDER 6 YEARS OF AGE: ASK A DOCTOR.

CONSUMERS WITH LIVER OR KIDNEY DISEASE: ASK A DOCTOR.

STORAGE AND HANDLING

STORE BETWEEN 20-25 DEGREES CELSIUS (67-77 DEGREES FAHRENHEIT)

PROTECT FROM FREEZING

INACTIVE INGREDIENT

FD&C BLUE #1, GELATIN, MONO AND DIGLYCERIDE OF CAPRYLIC/CAPRIC ACID, PHARMACEUTICAL INK, POLYSORBATE 80, POVIDONE, PURIFIED WATER, SORBITOL SORBITAN SOLUTION.